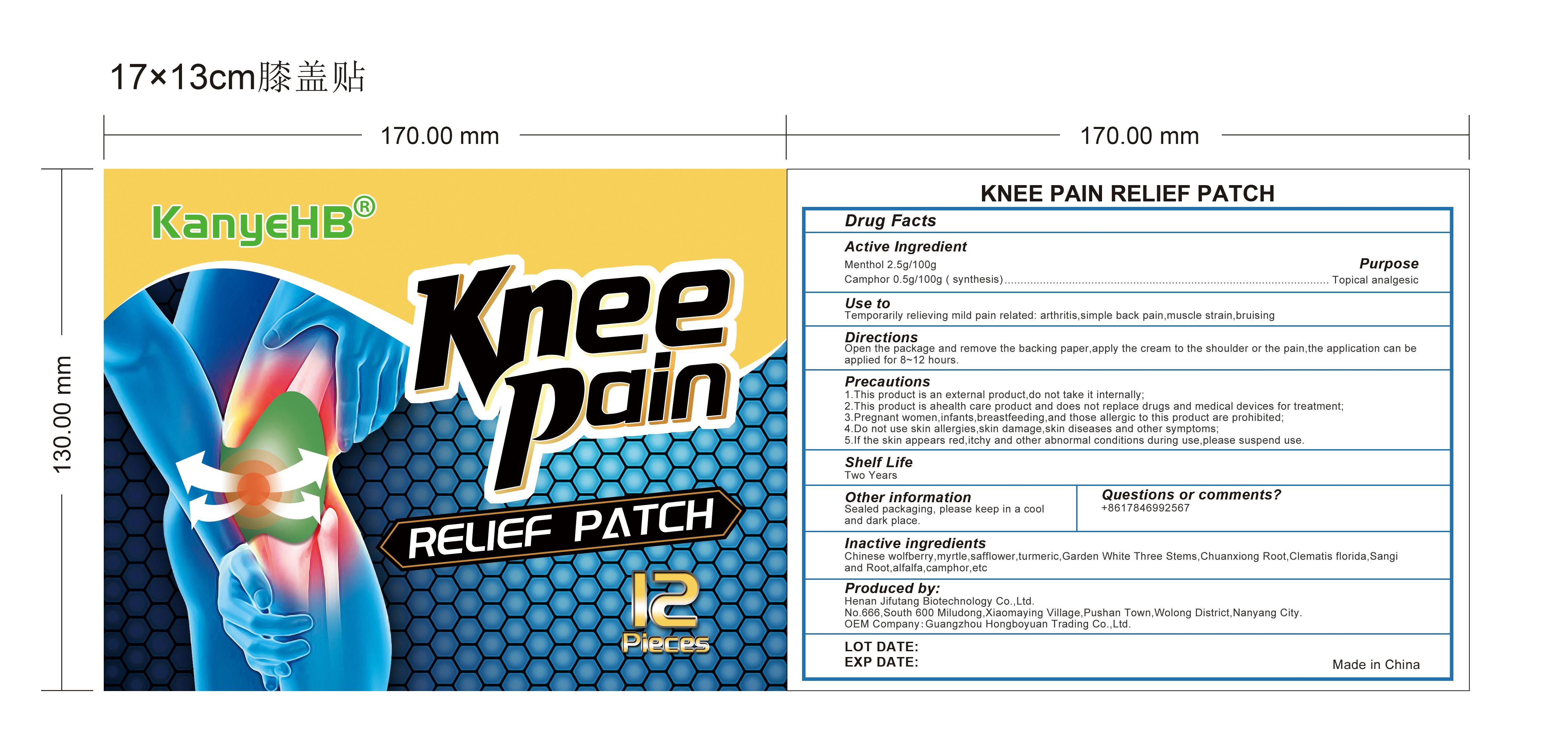 DRUG LABEL: Knee Pain Relief Patch
NDC: 83713-001 | Form: PATCH
Manufacturer: Guangzhou Hongboyuan Trading Co., Ltd.
Category: otc | Type: HUMAN OTC DRUG LABEL
Date: 20231012

ACTIVE INGREDIENTS: CAMPHOR (SYNTHETIC) 0.5 g/100 g; MENTHOL 2.5 g/100 g
INACTIVE INGREDIENTS: MYRRH; SAFFLOWER

Active ingredient: Menthol 2.5g/100g, Camphor 0.5g/100g （synthesis）

Purpose: Topical analgesic

INDICATIONS AND USAGE

Use to: Temporarily relieving mild pain related: arthritis, simple back pain, muscle strain, bruisinga

DOSAGE AND ADMINISTRATION

Directions: Open the package and remove the backing paper, apply the cream to the shoulder or the pain, the application can be applied for 8-12 hours.

WARNINGS

Precautions:

1. This product is an external product, do not take it internally;

2. This product is a health care product and does notreplace drugs and medical devices for treatment;

3. Pregnant women, infants, breastfeeding, and those allergic to this product are prohibited;

4. Do not use skin allergies, skin damage, skin diseases and other symptoms;

5. If the skin appears red, itchy and other abnormal conditions during use, please suspend use.

KEEP OUT OF REACH OF CHILDREN

Same as WARNINGS SECTION

Questions or comments? +8617846992567

INACTIVE INGREDIENT

Inactive ingredients: Chinese wolfberry, myrtle, safflower, turmeric, Garden White Three Stems, Chuanxiong Root, Clematis florida, Sanqi and Root, alfalfa, camphor, etc

STATEMENT OF IDENTITY

Produced by:
Henan Jifutang Biotechnology Co..Ltd.

No.666, South 600 Miludong, Xiaomaying Village, Pushan Town,Wolong District, Nanyang City.
OEM Company:Guangzhou Hongboyuan Trading Co.,Ltd.

STORAGE AND HANDLING

Shelf Life: Two Years

Other information: Sealed packaging, please keep in a cool and dark place.

PACKAGE LABEL

see labe